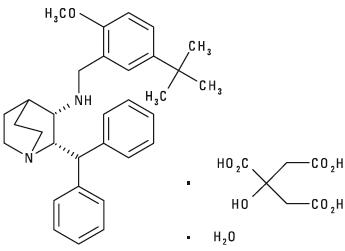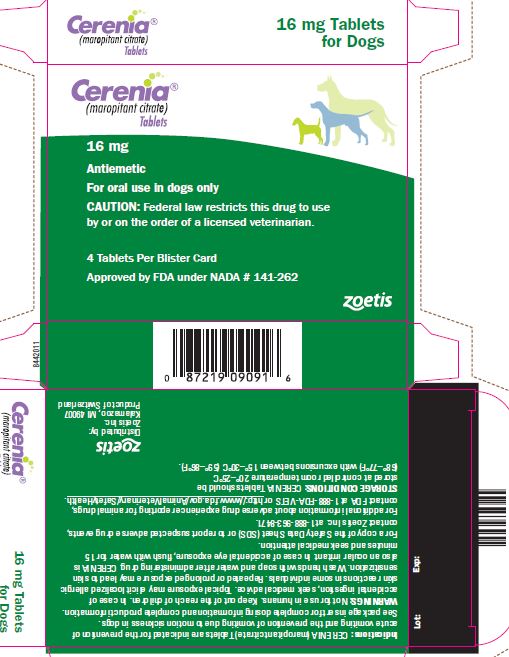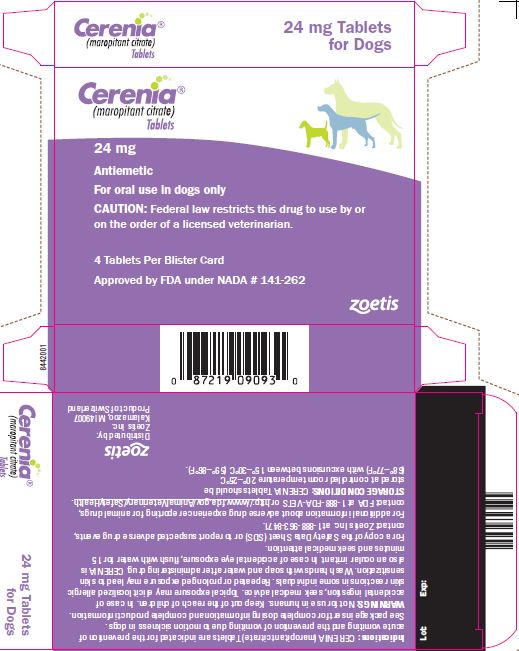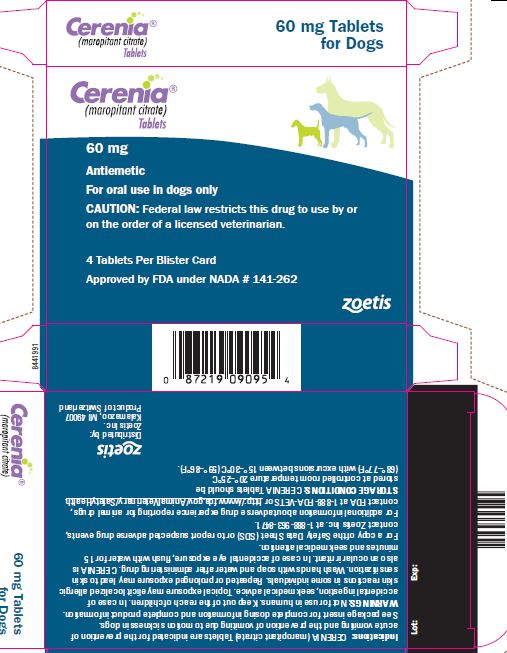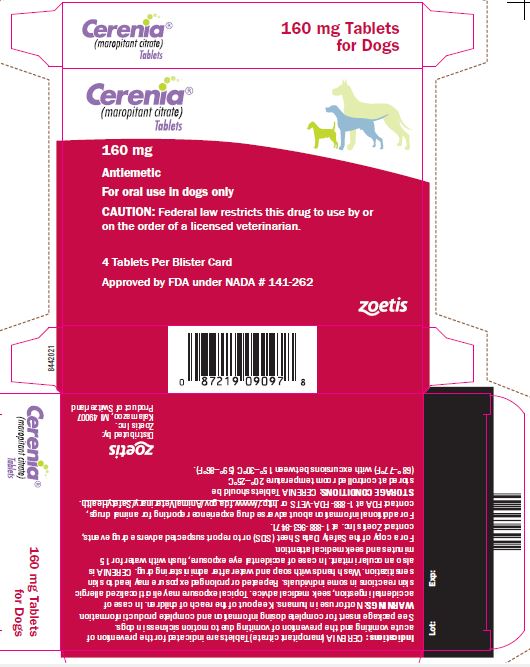 DRUG LABEL: Cerenia
NDC: 54771-8180 | Form: TABLET
Manufacturer: Zoetis Inc.
Category: animal | Type: PRESCRIPTION ANIMAL DRUG LABEL
Date: 20220831

ACTIVE INGREDIENTS: MAROPITANT CITRATE 16 mg/1 1

Cerenia®
(maropitant citrate)
Tablets

Antiemetic

For oral use in dogs only

Caution

Federal law restricts this drug to use by or on the order of a licensed veterinarian.

DESCRIPTION

Maropitant is a neurokinin (NK1) receptor antagonist that blocks the pharmacological action of substance P in the central nervous system (CNS). Maropitant is the non-proprietary designation for a substituted quinuclidine. The empirical formula is C32H40N2O C6H8O7 H2O and the molecular weight 678.81. The chemical name is (2S,3S)-2-benzhydryl-N-(5-tert-butyl-2-methoxybenzyl) quinuclidin-3-amine citrate monohydrate. Each peach-colored oval tablet is scored and contains 16, 24, 60 or 160 mg of maropitant as maropitant citrate per tablet.

The chemical structure of maropitant citrate is:

INDICATIONS

CERENIA (maropitant citrate) Tablets are indicated for the prevention of acute vomiting and the prevention of vomiting due to motion sickness in dogs.

DOSAGE AND ADMINISTRATION:

For Prevention of Acute Vomiting in dogs 2 -7 months of age: Administer CERENIA Tablets orally at a minimum dose of 2 mg/kg (0.9 mg/lb) body weight once daily for up to 5 consecutive days (see WARNINGS and Animal Safety).

For Prevention of Acute Vomiting in dogs 7 months of age and older: Administer CERENIA Tablets orally at a minimum dose of 2 mg/kg (0.9 mg/lb) body weight once daily until resolution of acute vomiting.

If vomiting persists despite treatment, the case should be re-evaluated. CERENIA is most effective in preventing acute vomiting associated with chemotherapy if administered prior to the chemotherapeutic agent.

For prevention of acute vomiting, dispense whole or half tablets in strength(s) that most closely result in a 2 mg/kg dose:

Dog body weight |  | Number of Tablets
Pounds | Kilograms | 16 mg | 24 mg | 60 mg
8 | 4 | ½
15 | 8 | 1
25 | 12 |  | 1
50 | 24 |  | 2
65 | 30 |  |  | 1
130 | 60 |  |  | 2

Interchangeable use with CERENIA Injectable Solution for Prevention of Acute Vomiting:

In dogs that are actively vomiting, to ensure that the full initial dose is administered, CERENIA Injectable Solution is recommended at a dose of 1 mg/kg once daily. (See package insert for CERENIA injectable solution.) Thereafter, for the prevention of acute vomiting, CERENIA Tablets at a dose of 2 mg/kg once daily may be used interchangeably with CERENIA Injectable Solution for up to 5 days.

For Prevention of Vomiting Due to Motion Sickness in dogs 4 months and older

For Prevention of Vomiting due to motion sickness in dogs 4 months of age and older: Administer CERENIA Tablets orally at a minimum dose of 8 mg/kg (3.6 mg/lb) body weight once daily for up to 2 consecutive days (see WARNINGS and Animal Safety).

Administer CERENIA Tablets a minimum of two hours prior to travel with a small amount of food to mitigate vomiting associated with administration of the dose on an empty stomach; however, refrain from feeding a full meal prior to travel.

Prevention of Vomiting Due to Motion Sickness in Dogs 4 months of age and older:

Dispense whole or half tablets in strengths that most closely result in an 8 mg/kg dose once daily for up to 2 consecutive days :

Dog body weight |  |  | Number of tablets
Pounds | Kilograms | 16mg | 24mg | 60mg | 160mg
2 | 1 | 1/2
3 | 1.5 |  | 1/2
4 | 2 | 1
6 | 3 |  | 1
8 | 4 | 2
13 | 6 |  | 2
16 | 7.5 |  |  | 1
22 | 10 |  |  |  | 1/2
33 | 15 |  |  | 2
44 | 20 |  |  |  | 1
66 | 30 |  |  |  | 1 1/2
88 | 40 |  |  |  | 2
132 | 60 |  |  |  | 3

CERENIA injectable solution should not be used interchangeably with CERENIA tablets for the prevention of vomiting due to motion sickness (8mg/kg).

WARNINGS

Not for use in humans. Keep out of the reach of children. In case of accidental ingestion, seek medical advice. Topical exposure may elicit localized allergic skin reactions in some individuals. Repeated or prolonged exposure may lead to skin sensitization. Wash hands with soap and water after administering drug. CERENIA is also an ocular irritant. In case of accidental eye exposure, flush with water for 15 minutes and seek medical attention.

In puppies younger than 11 weeks of age, histological evidence of bone marrow hypocellularity was observed at higher frequency and greater severity in puppies treated with CERENIA compared to control puppies. In puppies 16 weeks and older, bone marrow hypocellularity was not observed (see ANIMAL SAFETY).

PRECAUTIONS

The safe use of CERENIA Tablets has not been evaluated in dogs used for breeding, or in pregnant or lactating bitches.

The safe use of CERENIA has not been evaluated in dogs with gastrointestinal obstruction, or dogs that have ingested toxins.

Use with caution in dogs with hepatic dysfunction because CERENIA is metabolized by CYP3A enzymes (see Pharmacokinetics). Use with caution with other medications that are highly protein bound. The concomitant use of CERENIA with other protein bound drugs has not been studied in dogs. Commonly used protein bound drugs include NSAIDs, cardiac, anticonvulsant, and behavioral medications. The influence of concomitant drugs that may inhibit the metabolism of CERENIA has not been evaluated. Drug compatibility should be monitored in patients requiring adjunctive therapy.

CERENIA causes dose related decreases in appetite and body weight (see ANIMAL SAFETY). To maximize therapeutic potential of CERENIA, the underlying cause of vomiting should be identified and addressed in dogs receiving CERENIA.

ADVERSE REACTIONS

Prevention of Acute Vomiting (minimum of 2 mg/kg)

The following adverse reactions were reported during the course of a US field study for the prevention of acute vomiting in dogs treated with CERENIA Tablets at a minimum of 2 mg/kg orally and/or Injectable Solution at 1 mg/kg subcutaneously once daily for up to 5 consecutive days:

Frequency of Adverse Reactions by Treatment
Adverse Reaction | Placebo (n=69) |  | CERENIA (n=206)
Adverse Reaction | # dogs | % occurrence | # dogs | % occurrence
Death during study | 4 | 5.8 | 10 | 4.9
Euthanized during study | 0 | 0 | 2 | 1
Diarrhea | 6 | 8.7 | 8 | 3.9
Hematochezia/bloody stool | 5 | 7.2 | 4 | 1.9
Anorexia | 2 | 2.9 | 3 | 1.5
Otitis/Otorrhea | 0 | 0 | 3 | 1.5
Endotoxic Shock | 1 | 1.4 | 2 | 1
Hematuria | 0 | 0 | 2 | 1
Excoriation | 0 | 0 | 2 | 1

Other clinical signs were reported but were <0.5% of dogs.

Prevention of Vomiting Due to Motion Sickness (minimum of 8 mg/kg)

The following adverse reactions were reported during US studies for the prevention of vomiting due to motion sickness in dogs treated with CERENIA Tablets at a minimum of 8 mg/kg orally one time. Dogs may have experienced more than one of the observed adverse reactions.

Frequency of Adverse Reactions by Treatment
Adverse Reaction | Placebo (n=195) |  | CERENIA (n=208)
Adverse Reaction | # dogs | % occurrence | # dogs | % occurrence
Hypersalivation | 19 | 9.7 | 26 | 12.5
Vomiting* | 0 | 0 | 11 | 5.3
Muscle Tremors | 1 | 0.5 | 2 | 1
Sedation/Depression | 3 | 1.5 | 2 | 1
Retching | 3 | 1.5 | 1 | 0.5
Flatulence | 0 | 0 | 1 | 0.5

The following adverse reactions were reported during a European field study for the prevention of vomiting due to motion sickness in dogs treated with CERENIA Tablets at a minimum of 8 mg/kg orally once daily for 2 consecutive days. Dogs may have experienced more than one of the observed adverse reactions.

*Not associated with motion sickness.

Frequency of Adverse Reactions by Treatment
Adverse Reaction | Placebo (n=106) |  | CERENIA (n=107)
Adverse Reaction | # dogs | % occurrence | # dogs | % occurrence
Vomiting | 4 | 4 | 10 | 9
Drowsiness/Lethargy/Apathy | 1 | 1 | 8 | 8
Hypersalivation | 2 | 2 | 5 | 5
Anxiety | 0 | 0 | 2 | 2
Trembling/Tremors | 0 | 0 | 2 | 2
Inappetence | 0 | 0 | 2 | 2
Mucus in stool | 0 | 0 | 1 | 1

The following Adverse Reactions were reported during the conduct of a US clinical field trial where CERENIA Tablets were administered once daily for 28 consecutive days to 32 dogs: lethargy, vomiting, inappetence, corneal edema, and enlarged lymph nodes.

Post-Approval Experience (Revised May 2019)

The following adverse events are based on post-approval adverse drug experience reporting. Not all adverse events are reported to FDA CVM. It is not always possible to reliably estimate the adverse event frequency or establish a causal relationship to product exposure using these data.

The following adverse events reported for dogs are listed in decreasing order of frequency:
anorexia, depression/lethargy, hypersalivation, vomiting, diarrhea, trembling, ataxia, allergic reactions, weight loss, convulsion, hyperactivity, and panting.

Cases of ineffectiveness have been reported.

Cases of death (including euthanasia) have been reported.

To report suspected adverse events, for technical assistance or to obtain a copy of the SDS, contact Zoetis Inc. at 1-888-963-8471 or www.zoetis.com.

For additional information about adverse drug experience reporting for animal drugs, contact FDA at 1-888-FDA-VETS or online at http://www.fda.gov/AnimalVeterinary/SafetyHealth

CLINICAL PHARMACOLOGY

Pharmacokinetics

Mean (±SD) Plasma Pharmacokinetic Parameters for Maropitant in Beagle Dogs after single dose and repeat oral doses of Maropitant:

PK Parameter | 2 mg/kg Single; Dose | 2 mg/kg repeat Doses1 | 8 mg/kg Single; Dose | 8 mg/kg; repeat Doses1
Tmax2; (hr) | 2.0; (1.5 – 3.0) | 1.5; (1.0 – 3.0) | 1.5; (1.0 – 3.0) | 2.5; (1.5 – 7.0)
Cmax; (ng/mL) | 154; (111) | 304; (165) | 588; (416) | 1409; (516)
AUC(0-24); (ng*hr/mL) | 1440; (982) | 3890; (3030) | 6730; (5030) | 26600; (9200)
T1/22; (hr) | NC | 7.69; (6.21 - 17.8) | NC | 25.4; (6.06 - 30.0)
Accumulation Ratio (Rac)3 | NA | 2.46; (1.68, 3.61) | NA | 4.81; (3.28, 7.05)

^1Following once daily doses of maropitant for 14 days.

^2Median (Range)

^3Ratio=Multiple Dose AUC(0-24)/Single Dose AUC(0-24), Least square means (95% Confidence Interval)

NA= Not Applicable

NC= Not Calculated

Following oral administration, median time to reach Cmax was within 2.5 hr. The absolute bioavailability of maropitant was low (24%) following oral administration of 2 mg/kg maropitant. After an oral dose, prandial status does not significantly affect the extent of oral bioavailability. Greater than dose-proportional drug exposure can be expected with an increase in dose (1-16 mg/kg PO). However as doses increase (20-50 mg/kg PO), the dose proportionality is re-established. Based upon in vitro enzyme kinetics, involvement of a high capacity enzyme (CYP3A12) may contribute to this return to dose linearity. Due to dose dependent pharmacokinetics, the maropitant concentrations reached steady state approximately after 4 and 8 days following 2 and 8 mg/kg, respectively. The observed drug accumulation ratios were 2.46 and 4.81, after oral administration of 2 and 8 mg/kg, respectively. The exposure of 10 week old puppies to maropitant was lower than that observed in adult dogs, particularly after repeat doses of 1 or 2 mg/kg. Systemic clearance of maropitant following IV administration was 970, 995, and 533 mL/hr/kg at doses of 1, 2 and 8 mg/kg, respectively.

Urinary recovery of maropitant and its major metabolite was minimal (<1% each). The hepatic metabolism of maropitant involves two cytochrome P-450 isoenzymes: CYP2D15 and CYP3A12. In in vitro enzyme kinetics data suggest that the non-linear kinetics may be partially associated with saturation of the low capacity enzyme (CYP2D15). Plasma protein binding of maropitant was high (99.5%).

Pharmacodynamics

Vomiting is a complex process coordinated centrally by the emetic center which consists of several brainstem nuclei (area postrema, nucleus tractus solitarius, dorsal motor nucleus of the vagus) that receive and integrate sensory stimuli from central and peripheral sources and chemical stimuli from the circulation and the cerebro-spinal fluid. Maropitant is a neurokinin 1 (NK1) receptor antagonist which acts by inhibiting the binding of substance P, a neuropeptide of the tachykinin family. Substance P is found in significant concentrations in the nuclei comprising the emetic center and is considered the key neurotransmitter involved in emesis.^1 By inhibiting the binding of substance P within the emetic center, maropitant provides broad-spectrum effectiveness against neural (central) and humoral (peripheral) causes of vomiting. In vivo model studies in dogs have shown that maropitant has antiemetic effectiveness against both central and peripheral emetogens including apomorphine, and syrup of ipecac.

^1Diemunsch P, Grelot L. Potential of substance P antagonists as antiemetics. [Review] [60 refs]. Drugs. 2000;60:533-46.

EFFECTIVENESS

Prevention of Acute Vomiting

In laboratory model studies, CERENIA Tablets dosed at a minimum of 2 mg/kg BW reduced the number of emetic events associated with established neural (central) and humoral (peripheral) stimuli. Following administration of apomorphine (central emetic stimuli), vomiting was observed in 33% (4 of 12) of Beagle dogs treated with CERENIA Tablets and 100% (12 of 12) of Beagle dogs treated with placebo tablets. Following administration of syrup of ipecac (peripheral emetic stimuli) vomiting was observed in 33% (4 of 12) of Beagle dogs treated with CERENIA Tablets and in 83% (10 of 12) of Beagle dogs treated with placebo tablets.

In a study of 275 canine patients presented to veterinary hospitals with a history of acute vomiting, dogs were initially administered CERENIA Injectable Solution or placebo on Day 0. Following the initial dose, dogs allocated to the CERENIA group were treated with either CERENIA Tablets at a minimum of 2 mg/kg orally or Injectable Solution at 1 mg/kg subcutaneously once daily at the discretion of the clinician. Dogs allocated to the placebo group were treated using either an injectable placebo solution or placebo tablets once daily at the discretion of the clinician. Of the 199 dogs included in the analysis for effectiveness, 27 of 54 dogs (50%) in the placebo group displayed vomiting at some time during the study and 31 of 145 dogs (21.4%) in the treated group displayed vomiting during the study period.

Percent Of Vomiting For Each Study Day, Based Upon Treatment And Route Of Administration.
Days | Treatment | Route | # dogs | # vomited | % vomited
Day 0 | Placebo (54) | SC | 54 | 15 | 28%
 | CERENIA (145) | SC | 145 (143 [2 dogs administered CERENIA were not observed on Day 0. Their vomiting status was unknown. 143 was used in the denominator for % vomited.]) | 14 | 10%
Day 1 | Placebo (45) | PO | 22 | 3 | 14%
Day 1 | Placebo (45) | SC | 23 | 16 | 70%
Day 1 | CERENIA (108) | PO | 67 | 2 | 3%
Day 1 | CERENIA (108) | SC | 41 | 16 | 39%
Day 2 | Placebo (16) | PO | 7 | 2 | 29%
Day 2 | Placebo (16) | SC | 9 | 6 | 67%
Day 2 | CERENIA (37) | PO | 24 | 0 | 0%
Day 2 | CERENIA (37) | SC | 13 | 8 | 62%
Day 3 | Placebo (6) | PO | 2 | 0 | 0%
Day 3 | Placebo (6) | SC | 4 | 1 | 25%
Day 3 | CERENIA (21) | PO | 14 | 0 | 0%
Day 3 | CERENIA (21) | SC | 7 | 5 | 71%
Day 4 | Placebo (2) | PO | 1 | 0 | 0%
Day 4 | Placebo (2) | SC | 1 | 1 | 100%
Day 4 | CERENIA (7) | PO | 5 | 0 | 0%
Day 4 | CERENIA (7) | SC | 2 | 1 | 50%
Day 5 | CERENIA (1) | SC | 1 | 0 | 0%

*2 dogs administered CERENIA were not observed on Day 0. Their vomiting status was unknown. 143 was used in the denominator for % vomited.

In US field studies in veterinary patients, CERENIA Tablets and Injectable Solution were well tolerated in dogs presenting with various conditions including parvovirus, gastroenteritis, and renal disease. There were no notable differences in mean laboratory values between CERENIA-treated and placebo-treated patients.

CERENIA Tablets were used safely in dogs receiving other frequently used veterinary products such as fluid and electrolyte replacement solutions, antimicrobial agents, vaccines, antacids, and antiparasitic agents

Prevention of Vomiting due to Motion Sickness

In a study of canine veterinary patients taken on a one-hour car journey and treated with either CERENIA Tablets at a minimum dose of 8 mg/kg BW or placebo tablets 2 hours prior to the journey, 67 of 122 (55%) of dogs vomited during the journey when treated with placebo while 8 of 122 (7%) vomited during the journey after treatment with CERENIA Tablets. The probability that a dog in this study, prone to motion sickness would NOT vomit during a journey if treated with CERENIA Tablets was 93%, while the probability was 48% if treated with placebo.

ANIMAL SAFETY

Laboratory and field studies have demonstrated that CERENIA Tablets are well tolerated in dogs after oral administration.

Target Animal Safety Study for Acute Vomiting

Fifty six Beagle dogs (28 males and 28 females) approximately 16 weeks of age were administered CERENIA Tablets orally once daily for 15 days at 0, 2, 6, and 10 mg/kg. There were 8 dogs (4 males and 4 females) in the 2 mg/kg group and 16 dogs (8 males and 8 females) in all other groups. CERENIA Tablets caused decreases in food consumption and body weight that were not dose-dependent and did not persist after cessation of treatment.

Beagle dogs approximately 8 weeks of age were administered CERENIA Tablets orally once daily for 15 days at 0, 2, 6, and 10 mg/kg using a protocol similar to the previous study. A dose dependent increase in severity of bone marrow hypoplasia was observed histologically. Interpretation of these study results is complicated by the health status of study animals. Dogs used in the study were weaned early, minimally acclimated to the test facility, many of the dogs in the study tested positive for coccidia and some tested positive for canine parvovirus.

Beagle dogs approximately 10 weeks of age were administered either placebo tablets for 2 days, CERENIA Tablets at 8 mg/kg for 2 days, placebo (saline) subcutaneously (SC) for 5 days, CERENIA Injectable Solution at 1 mg/kg SC for 5 days, or CERENIA Tablets at 2 mg/kg for 5 days (8 dogs in each dose group). Mild pain associated with injection was noted in more dogs and lasted longer in dogs that received maropitant injections compared to saline. Males administered CERENIA at 8 mg/kg orally for 2 days had a decrease in food consumption. Body weight and food consumption were variable throughout the 4 week acclimation period. Two dogs that received 8 mg/kg maropitant orally for 2 days were below the reference range for reticulocyte counts. Decreases in reticulocyte counts were also seen in 4 (of 8) placebo treated dogs (SC saline for 5 days). Hypocellular femoral bone marrow described as "minimal" was seen in 1 male that received 1 mg/kg maropitant SC for 5 days; reticulocyte counts were not available for this dog.

Twenty four Beagle dogs (12 males and 12 females) 7 months of age were administered maropitant at doses of 0, 1, 5, and 20 mg/kg orally once daily for 93 consecutive days. Maropitant produced sporadic clinical signs (salivation, emesis), body weight loss, and lower serum albumin levels at 20 mg/kg/day.

Maropitant increased P-R interval, P wave duration, and QRS amplitude in the 20 mg/kg /day dose group.

One female in the 20 mg/kg/day group had increased cellularity of the bone marrow. This female was noted to have lower mean red cell parameters (red blood cell count, hemoglobin, hematocrit) and higher platelet counts and reticulocytes.

Target Animal Safety Study for Motion Sickness

Forty Beagle dogs (20 males and 20 females) between 16 – 18 weeks of age were administered CERENIA Tablets orally once daily for 6 days at 0, 8 and 24 mg/kg. There were 16 dogs (8 males and 8 females) in the 0 and 24 mg/kg groups and 8 dogs (4 males and 4 females) in the 8 mg/kg group. At 24 mg/kg, CERENIA Tablets caused decreases in food consumption, with decreases in body weight, liver and testis weight; and an increase in RBC count indicating hemoconcentration, but the effects on feed consumption, body weight, and RBCs did not persist in the post-treatment recovery period (beyond Day 5).

Beagle dogs approximately 8 weeks of age were administered CERENIA Tablets orally once daily for 6 days at 0, 8, and 24 mg/kg using a protocol similar to the previous study. One dog in the 24 mg/kg/day group died of unknown causes on study day 2 and a dose dependent increase in occurrence and severity of bone marrow hypoplasia and lymphoid depletion was observed histologically. Interpretation of these study results is complicated by the health status of study animals. Dogs used in the study were weaned early, minimally acclimated to the test facility, and many of the dogs in the study tested positive for coccidia. Additionally, some dogs in the study tested positive for canine parvovirus, however, clinical parvoviral disease was not definitively diagnosed.

Tolerance Studies

Twenty four Beagle dogs (14 males and 10 females) between 11 and 25 weeks of age were administered CERENIA Tablets in 2 phases with 8 dogs per group. In the first phase the dogs were administered 0, 20 or 30 mg/kg orally once daily for 7 days and in the second phase 0, 40, or 50 mg/kg once daily for 7 days.
CERENIA Tablets administered at 20 and 30 mg/kg caused occasional vomiting. CERENIA Tablets administered at 40 mg/kg and 50 mg/kg caused clinically relevant signs of weight loss, vomiting, soft stools, weakness, lethargy, salivation and hypokalemia. Additionally, leukopenia characterized by a neutropenia and a trend toward decreasing plasma phosphorus values was seen. Decreased heart rate and prolonged corrected QT intervals were seen in all treatment groups in a dose dependent manner.

Twenty-four Beagle dogs (12 males and 12 females) approximately 28 weeks of age were administered maropitant (mesylate salt) orally once daily for 90 days at 0, 1, 5, and 20 mg/kg. End of study body weights in the 20 mg/kg group were 8-15% lower than baseline body weights.

STORAGE CONDITIONS

CERENIA Tablets should be stored at controlled room temperature 20°–25°C (68°–77°F) with excursions between 15°–30°C (59°–86°F).

HOW SUPPLIED

CERENIA peach-colored tablets are scored with a break line, and contain 16, 24, 60 or 160 mg of maropitant as maropitant citrate per tablet. Each tablet is marked with "MPT" and the tablet strength. Each tablet size is packaged in a bottle containing 60 tablets and packaged in blister packs containing 4 tablets per perforated sheet.

Approved by FDA under NADA # 141-262

zoetis

Distributed by:
Zoetis Inc.
Kalamazoo, MI 49007

Product of Ireland

Revised: January 2020

8838170